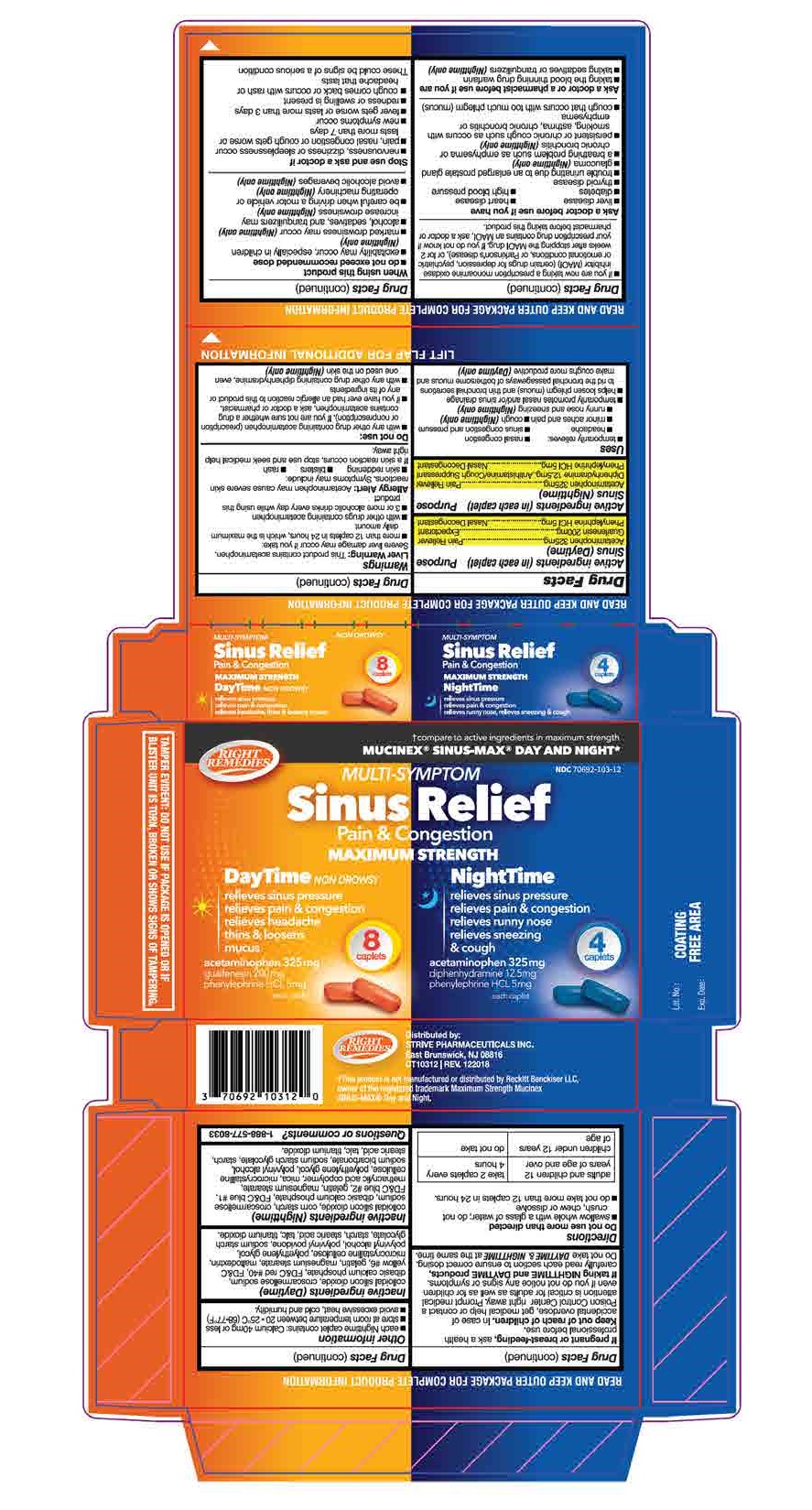 DRUG LABEL: Multi Symptom Sinus Relief Pain and Congestion Daytime Nighttime
NDC: 70692-103 | Form: KIT | Route: ORAL
Manufacturer: Strive Pharmaceuticals Inc.
Category: otc | Type: HUMAN OTC DRUG LABEL
Date: 20201116

ACTIVE INGREDIENTS: GUAIFENESIN 200 mg/1 1; ACETAMINOPHEN 325 mg/1 1; PHENYLEPHRINE HYDROCHLORIDE 5 mg/1 1; PHENYLEPHRINE HYDROCHLORIDE 5 mg/1 1; DIPHENHYDRAMINE HYDROCHLORIDE 12.5 mg/1 1; ACETAMINOPHEN 325 mg/1 1
INACTIVE INGREDIENTS: DIBASIC CALCIUM PHOSPHATE DIHYDRATE; POLYETHYLENE GLYCOL 400; POLYVINYL ALCOHOL, UNSPECIFIED; CELLULOSE, MICROCRYSTALLINE; STEARIC ACID; SODIUM STARCH GLYCOLATE TYPE A CORN; TALC; POVIDONE; STARCH, CORN; GELATIN; CROSCARMELLOSE SODIUM; MALTODEXTRIN; MAGNESIUM STEARATE; SILICON DIOXIDE; FD&C YELLOW NO. 6; FD&C RED NO. 40; TITANIUM DIOXIDE; MAGNESIUM STEARATE; POLYETHYLENE GLYCOL 400; FD&C BLUE NO. 2; TALC; SODIUM STARCH GLYCOLATE TYPE A CORN; SILICON DIOXIDE; STARCH, WHEAT; STEARIC ACID; POLYVINYL ALCOHOL, UNSPECIFIED; MICA; TITANIUM DIOXIDE; FD&C BLUE NO. 1; METHACRYLIC ACID - METHYL METHACRYLATE COPOLYMER (1:1); SODIUM BICARBONATE; CELLULOSE, MICROCRYSTALLINE; DIBASIC CALCIUM PHOSPHATE DIHYDRATE; STARCH, CORN; GELATIN; CROSCARMELLOSE SODIUM

MULTI-SYMPTOM SINUS RELIEF
PAIN & CONGESTION
MAXIMUM STRENGTH DAYTIME AND NIGHTTIME

Active ingredients (in each caplet) (Daytime) | Purpose
Acetaminophen 325mg | Pain Reliever
Guaifenesin 200mg | Expectorant
Phenylephrine HCl 5mg | Nasal Decongestant

Active ingredients (in each caplet) (Nighttime) | Purpose
Acetaminophen 325mg | Pain Reliever
Diphenhydramine 12.5mg | Anthistamine/Cough suppressant
Phenylephrine HCl 5mg | Nasal Decongestant

PURPOSE

Daytime

Pain reliever, Expectorant and Nasal decongestant

Nighttime

Pain reliever, Antihistamine/cough suppressant and Nasal decongestant

INDICATIONS AND USAGE

* temporarily relieves:

- nasal congestion
- headache
- minor aches and pain
- sinus congestion and pressure
- runny nose and sneezing (Nighttime only)
- cough (Nighttime only)

* temporarily promotes nasal and/or sinus drainag

* helps loosen phlegm (mucus) and thin bronchial secretions to rid the bronchial passageways of bothersome mucus and make coughs more productive (Daytime only)

WARNINGS

Liver warning:
This product contains acetaminophen. Severe liver damage may occur if you take:
*more than 12 caplets in 24 hrs, which is the maximum daily amount
* with other drugs containing acetaminophen
*3 or more alcoholic drinks every day while using this product
Allergy alert:
Acetaminophen may cause severe skin reactions. Symptoms may include:
*skin reddening
*blisters
*rash
If a skin reaction occurs, stop use and seek medical help right away.

Do not use
*with any other drug containing acetaminophen (prescription or nonprescription). If you are not sure whether a drug contains acetaminophen, ask a doctor or pharmacist.
* if you have ever had an allergic reaction to this product or any of its ingredients
* with any other drug containing diphenhydramine, even one used on the skin (Nighttime only)
* if you are now taking a prescription monoamine oxidase inhibitor (MAOI) (certain drugs for depression, psychiatric or emotional conditions, or Parkinson's disease), or for 2 weeks after stopping the MAOI drug. If you do not know if your prescription drug contains an MAOI, ask a doctor or pharmacist before taking this product.

Ask a doctor before use if you have

* liver disease
* heart disease
* diabetes
* high blood pressure
* thyroid disease
* trouble urinating due to an enlarged prostate gland
* glaucoma (Nighttime only)
* a breathing problem such as emphysema or chronic bronchitis (Nighttime only)
* persistent or chronic cough such as occurs with smoking, asthma, chronic bronchitis or emphysema
* cough that occurs with too much phlegm (mucus)

Ask a doctor or a pharmacist before use if you are
* taking the blood thinning drug warfarin
* taking sedatives or tranquilizers (Nighttime only)
When using this product
* do not exceed recommended dose
* excitability may occur, especially in children (Nighttime only)
* marked drowsiness may occur (Nighttime only)
* alcohol, sedatives, and tranquilizers may increase drowsiness (Nighttime only)
* be careful when driving a motor vehicle or operating machinery (Nighttime only)
* avoid alcoholic beverages (Nighttime only)

Stop use and ask a doctor if
* nervousness, dizziness, or sleeplessness occur
* pain, nasal congestion, or cough gets worse or lasts more than 7 days
* new symptoms occur
* fever gets worse or lasts more than 3 days
* redness or swelling is present
* cough comes back or occurs with rash or headache that lasts
These could be signs of a serious condition

If pregnant or breast-feeding,
ask a health professional before use.
Keep out of reach of children
In case of accidental overdose, get medical help or contact a Poison Control Center right away. Prompt medical attention is critical for adults as well as for children even if you do not notice any signs or symptoms.

If taking Nighttime and Daytime products,
carefully read each section to ensure correct dosing
Do not take DAYTIME and NIGHTTIME at the same time

Keep out of reach of children
In case of accidental overdose, get medical help or contact a Poison Control Center right away. Prompt medical attention is critical for adults as well as for children even if you do not notice any signs or symptoms.

Directions
* Do not use more than directed
* swallow whole with a glass of water; do not crush, chew or dissolve
* do not take more than 12 caplets in 24 hours

adults and children 12 years of age and over | take 2 caplets every 4 hours
children under 12 years of age | do not take

Other information
* each Nighttime caplet contains: Calcium 40mg or less
* store at room temperature 25°C (77°F) ; excursions permitted between 15°C - 30°C (59°F -86°F)

Inactive ingredients (Daytime)
microcrystalline cellulose, dibasic calcium phosphate, croscarmellose sodium, talc, colloidal silicon dioxide, stearic acid, magnesium stearate, polyvinyl alcohol, polyethylene glycol, titanium dioxide,FD&C yellow #6, FD&C red #40, gelatin, starch, polyvinyl povidone, maltodextrin, sodium starch glycolate

Inactive ingredients (Nightime)
microcrystalline cellulose, dibasic calcium phosphate, corn starch, croscarmellose sodium, talc, colloidal silicon dioxide, stearic acid, magnesium stearate, polyvinyl alcohol, polyethylene glyocol, mica, titanium dioxide, FD&C blue #1, methacrylic acid copolymer, FD&C blue #2, sodium bicarbonate, starch, gelatin, sodium starch glycolate